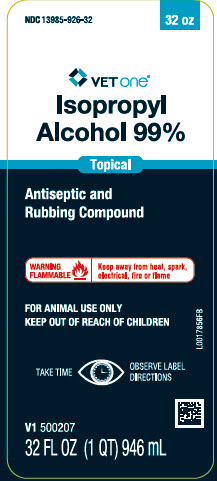 DRUG LABEL: Isopropyl Alcohol
NDC: 13985-926 | Form: SOLUTION
Manufacturer: MWI/VETONE
Category: animal | Type: OTC ANIMAL DRUG LABEL
Date: 20250317

ACTIVE INGREDIENTS: ISOPROPYL ALCOHOL 99 mL/100 mL
INACTIVE INGREDIENTS: WATER

Vetone 112.000/112AA/883AA
Isopropyl Alcohol 99%

Ingredients

ACTIVE INGREDIENT: Isopropyl alcohol 99%

INACTIVE INGREDIENT: Water

Indications and Use

INDICATIONS: Solution for use by veterinarians and artificial inseminators as a bactericide, disinfectant, rubefacient, and as a rub down in animals.

DIRECTIONS FOR USE: Use as topical antiseptic or for disinfection of instruments. May be used as a rub down in animals. Apply directly to affected area, wet thoroughly and massage briskly to stimulate circulation.

Warnings

WARNING: For external use only. If taken internally, serious gastric disturbance will result. Avoid contact with eyes. In case of eye contact, flush thoroughly with water. May be fatal if swallowed. In case of ingestion, seek medical attention.

FLAMMABLE: Do not use near heat or open flame.

Storage

Store at controlled room temperature between 15° – 30° C (59° – 86° F). Keep container tightly closed when not in use.

Adverse event

Distributed by: MWI, Boise, ID 83705

www.VetOne.net

Principal Display Panel

NDC 13985-926-32

VetOne

Isopropyl Alcohol 99%

Antiseptic and Rubbing Compound

WARNING FLAMMABLE. Keep away from heat, spark, electrical, fire or flame.

FOR ANIMAL USE ONLY

KEEP OUT OF REACH OF CHILDREN

Take time. Observe label directions

32 FL OZ (1 QT) (946 mL)